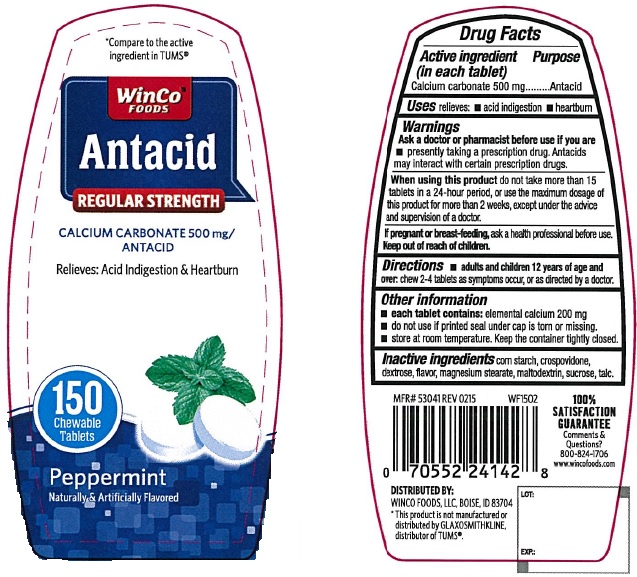 DRUG LABEL: Antacid
NDC: 67091-225 | Form: TABLET, CHEWABLE
Manufacturer: WinCo Foods, LLC
Category: otc | Type: HUMAN OTC DRUG LABEL
Date: 20220113

ACTIVE INGREDIENTS: CALCIUM CARBONATE 500 mg/1 1
INACTIVE INGREDIENTS: STARCH, CORN; CROSPOVIDONE; DEXTROSE, UNSPECIFIED FORM; MAGNESIUM STEARATE; MALTODEXTRIN; SUCROSE; TALC

Antacid Regular Strength Peppermint Tablets

Active ingredient (in each tablet)

Calcium carbonate 500 mg

Purpose

Antacid

Uses

relieves

- acid indigestion
- heartburn

Warnings

Ask a doctor or pharmacist before use if you are

- presently taking a prescription drug. Antacids may interact with certain prescription drugs.

When using this product

do not take more than 15 tablets in a 24-hour period, or use the maximum dosage of this product for more than 2 weeks, except under the advice and supervision of a doctor.

Keep out of reach of children.

Directions

- chew 2-4 tablets as symptoms occur, or as directed by a doctor.

Other information

- do not use if printed seal under the cap is torn or missing.
- store at room temperature.

Inactive ingredients

corn starch, crospovidone, dextrose, flavor, magnesium stearate, maltodextrin, sucrose, talc

Principal Display Panel

*Compare to the active ingredient in TUMS®

WinCo Foods

Anatcid

Regular Strength

CALCIUM CARBONATE 500 mg/ANTACID

Relieves: Acid Indigestion & Heartburn

150 Chewable Tablets

Peppermint

Naturally and Artificially Flavored